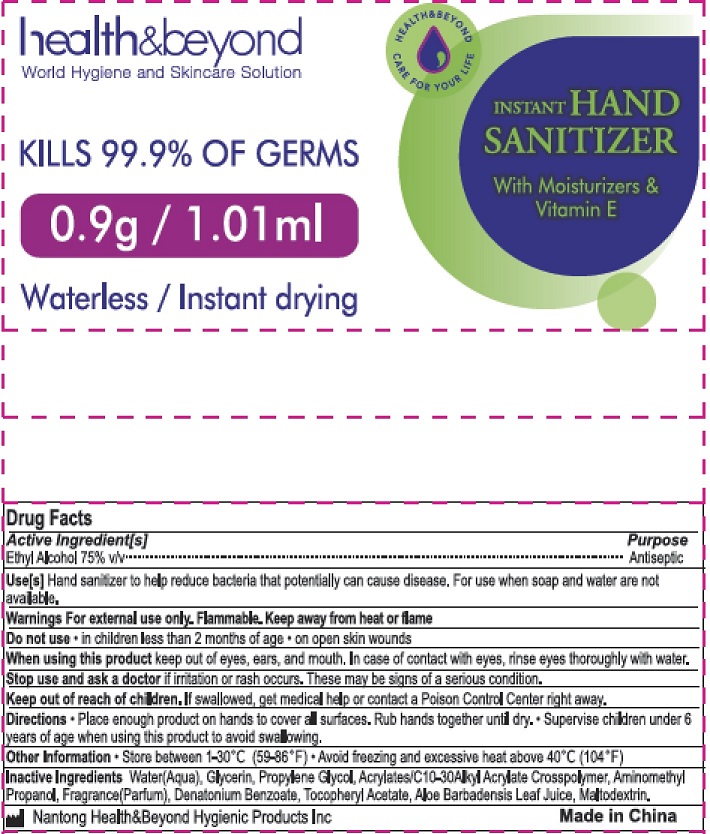 DRUG LABEL: Hand Sanitizer
NDC: 43473-009 | Form: GEL
Manufacturer: Nantong Health & Beyond Hygienic Products Inc.
Category: otc | Type: HUMAN OTC DRUG LABEL
Date: 20200703

ACTIVE INGREDIENTS: ALCOHOL 75 mL/100 mL
INACTIVE INGREDIENTS: MALTODEXTRIN; PROPYLENE GLYCOL; WATER; ALOE VERA LEAF; GLYCERIN; CARBOMER INTERPOLYMER TYPE A (55000 CPS); .ALPHA.-TOCOPHEROL ACETATE; AMINOMETHYLPROPANOL; DENATONIUM BENZOATE

Active Ingredient[s]
Ethyl Alcohol 75% v/v

Purpose
Antiseptic

INDICATIONS AND USAGE

Use[s]

Hand sanitizer to help reduce bacteria that potentially can cause disease. For use when soap and water are not available.

Warnings

For external use only. Flammable. Keep away from heat or flame

Do not use

• in children less than 2 months of age

• on open skin wounds

When using this product keep out of eyes, ears, and mouth. In case of contact with eyes, rinse eyes thoroughly with water.

Stop use and ask a doctor if irritation or rash occurs. These may be signs of a serious condition.

Keep out of reach of children. If swallowed, get medical help or contact a Poison Control Center right away.

Directions

• Place enough product on hands to cover all surfaces. Rub hands together until dry.

• Supervise children under 6 years of age when using this product to avoid swallowing.

Other information

• Store between 1 – 30°C (59- 86°F)

• Avoid freezing and excessive heat above 40°C (104°F)

Inactive Ingredients

Water (Aqua), Glycerin, Propylene Glycol, Acrylates/C10-30 Alkyl Acrylate Crosspolymer, Aminomethyl Propanol, Fragrance (Parfum), Denatonium Benzoate, Tocopheryl Acetate, Aloe Barbadensis Leaf Juice, Maltodextrin.